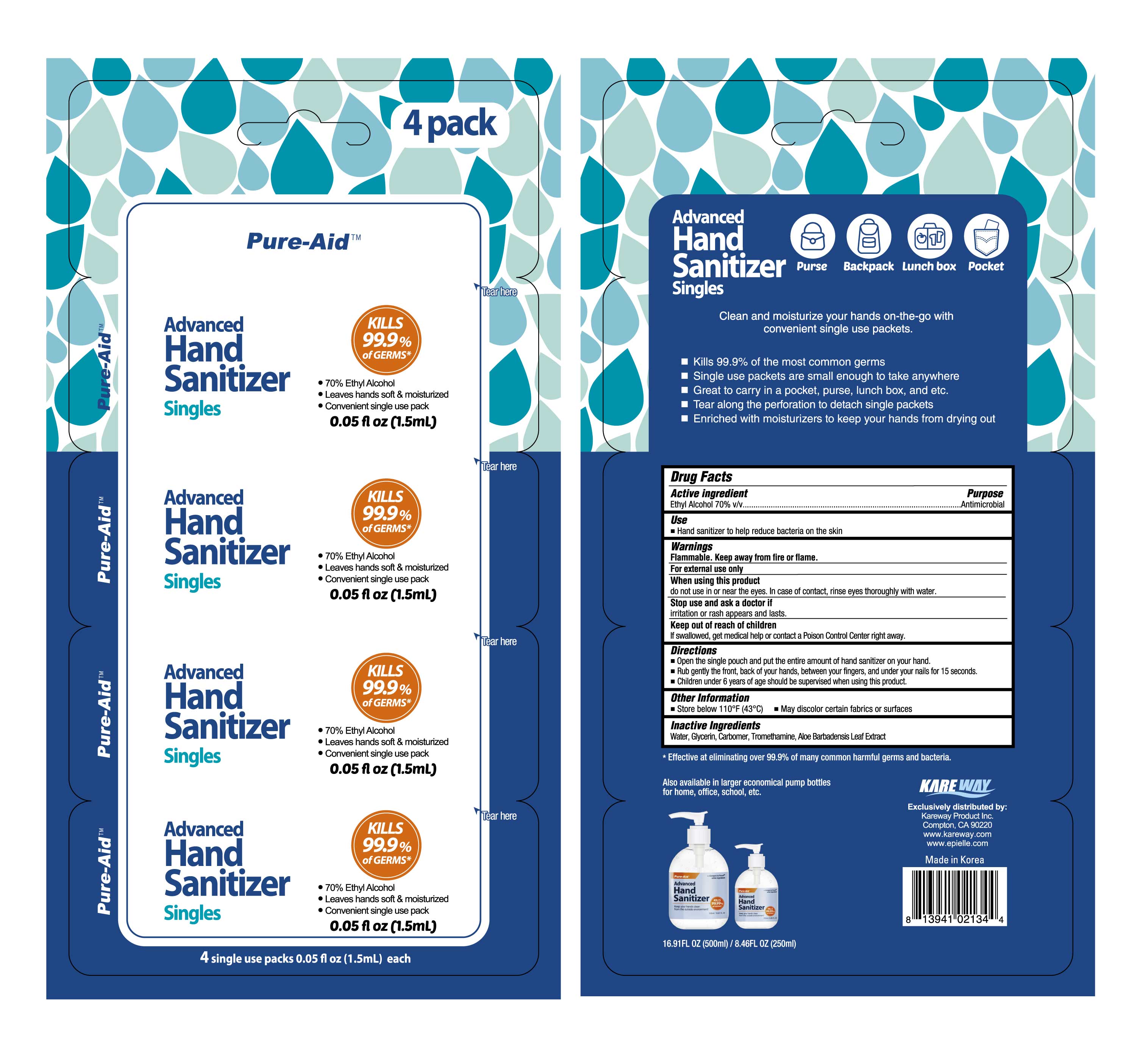 DRUG LABEL: Advanced Hand Sanitizer Singles
NDC: 67510-2134 | Form: LIQUID
Manufacturer: Kareway Product, Inc.
Category: otc | Type: HUMAN OTC DRUG LABEL
Date: 20200925

ACTIVE INGREDIENTS: ALCOHOL 70 mL/100 mL
INACTIVE INGREDIENTS: WATER; CARBOMER 980; GLYCERIN; TROMETHAMINE; ALOE VERA LEAF

Pure-Aid Advanced Hand Sanitizer Singles

Active Ingredient

Ethyl Alcohol 70% v/v

Purpose

Antimicrobial

Use

Hand sanitizer to help reduce bacteria on the skin

Warnings

Flammable, Keep away from fire or flame.

For external use only.

When using this product

do not use in or near the eyes. In case of contact, rinse eyes thoroughly with water

Stop use and ask a doctor if

irritation or rash appears and lasts

Keep out of reach of children

If swallowed, get medical help or contact or contact a Poison Control Center right away

Directions

- Open the single pouch and put the entire amount of hand sanitizer on your palm.
- Rub hands briskly until dry for about 15 seconds.
- Children under 6 years of age should be supervised when using this product.

Other Information

- Store below 110ºF (43ºC)

Inactive Ingredients

Water, Glycerin, Carbomer, Tromethamine, Aloe Barbadensis Leaf Extract